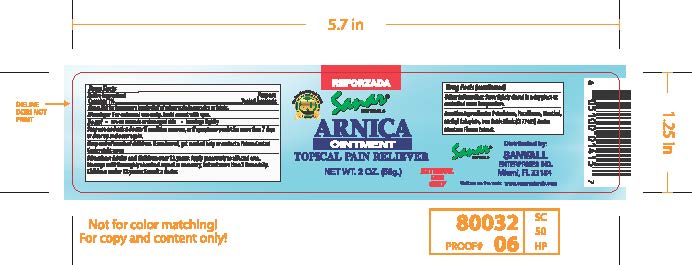 DRUG LABEL: Sanar Naturals Arnica Reforzada
NDC: 73386-150 | Form: OINTMENT
Manufacturer: Sanvall Enterprises, Inc
Category: otc | Type: HUMAN OTC DRUG LABEL
Date: 20241031

ACTIVE INGREDIENTS: CAMPHOR (SYNTHETIC) 1 mg/1 g
INACTIVE INGREDIENTS: FERROSOFERRIC OXIDE; METHYL SALICYLATE; PETROLATUM; ARNICA MONTANA FLOWER; MENTHOL; PARAFFIN

Sanar Naturals Arnica Ointment Reforzada

Active ingredient

Camphor 1%

Purpose

Topical Analgesic

Uses

Aid for temporary relief of minor pain of muscles or joints

Warnings

For external use only

Avoid contact with eyes.

Do not

use on wounds or damaged skin

bandage tightly

Stop use and ask a doctor if

condition worsens, or if symptoms persist for more than 7 days or clear up and occur again.

Keep out of reach of children.

is swallowed, get medical help or contact Poison Control Center right away

Directions

- Adults and children over 12 years: Apply to affected area. Massage until absorbed. Repeat as necessary, but not more than 3 times daily.
- Children under 12 years: Consult a doctor.

Other Information

Store tightly closed in a dry place at controlled room temperature

Inactive ingredients

Petrolatum, Paraffinum, Menthol, Methyl Salicylate, Iron Oxide Black (CI 77499), Arnica Montana Flower Extract.